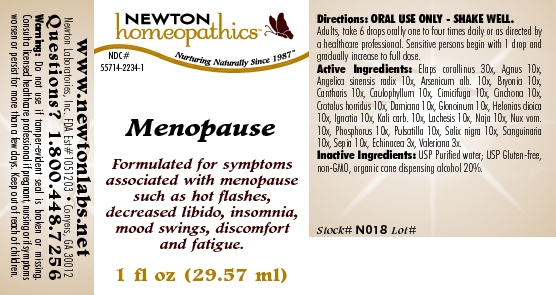 DRUG LABEL: Menopause 
NDC: 55714-2234 | Form: LIQUID
Manufacturer: Newton Laboratories, Inc.
Category: homeopathic | Type: HUMAN OTC DRUG LABEL
Date: 20110301

ACTIVE INGREDIENTS: Micrurus Corallinus Venom 30 [hp_X]/1 mL; Chaste Tree 10 [hp_X]/1 mL; Angelica Sinensis Root 10 [hp_X]/1 mL; Arsenic Trioxide 10 [hp_X]/1 mL; Bryonia Alba Root 10 [hp_X]/1 mL; Lytta Vesicatoria 10 [hp_X]/1 mL; Caulophyllum Thalictroides Root 10 [hp_X]/1 mL; Black Cohosh 10 [hp_X]/1 mL; Cinchona Officinalis Bark 10 [hp_X]/1 mL; Crotalus Horridus Horridus Venom 10 [hp_X]/1 mL; Turnera Diffusa Leafy Twig 10 [hp_X]/1 mL; Nitroglycerin 10 [hp_X]/1 mL; Chamaelirium Luteum Root 10 [hp_X]/1 mL; Strychnos Ignatii Seed 10 [hp_X]/1 mL; Potassium Carbonate 10 [hp_X]/1 mL; Lachesis Muta Venom 10 [hp_X]/1 mL; Naja Naja Venom 10 [hp_X]/1 mL; Strychnos Nux-vomica Seed 10 [hp_X]/1 mL; Phosphorus 10 [hp_X]/1 mL; Pulsatilla Vulgaris 10 [hp_X]/1 mL; Salix Nigra Bark 10 [hp_X]/1 mL; Sanguinaria Canadensis Root 10 [hp_X]/1 mL; Sepia Officinalis Juice 10 [hp_X]/1 mL; Echinacea, Unspecified 3 [hp_X]/1 mL; Valerian 3 [hp_X]/1 mL
INACTIVE INGREDIENTS: Alcohol

Menopause

INDICATIONS & USAGE SECTION

Menopause Formulated for symptoms associated with menopause such as hot flashes, decreased libido, insomnia, mood swings, discomfort and fatigue.

DOSAGE & ADMINISTRATION SECTION

Directions: ORAL USE ONLY - SHAKE WELL. Adults, take 6 drops orally one to four times daily or as directed by a healthcare professional. Sensitive persons begin with 1 drop and gradually increase to full dose.

OTC - ACTIVE INGREDIENT SECTION

Elaps corallinus 30x, Agnus 10x, Angelica sinensis radix 10x, Arsenicum alb. 10x, Bryonia 10x, Cantharis 10x, Caulophyllum 10x, Cimicifuga 10x, Cinchona 10x, Crotalus horridus 10x, Damiana 10x, Glonoinum 10x, Helonias dioica 10x, Ignatia 10x, Kali carb. 10x, Lachesis 10x, Naja 10x, Nux vom.10x, Phosphorus 10x, Pulsatilla 10x, Salix nigra 10x, Sanguinaria 10x, Sepia 10x, Echinacea 3x, Valeriana 3x.

OTC - PURPOSE SECTION

Formulated for symptoms associated with menopause such as hot flashes, decreased libido, insomnia, mood swings, discomfort and fatigue.

INACTIVE INGREDIENT SECTION

Inactive Ingredients: USP Purified Water; USP Gluten-free, non-GMO, organic cane dispensing alcohol 20%.

QUESTIONS SECTION

www.newtonlabs.net Newton Laboratories, Inc. FDA Est # 1051203 - Conyers, GA 30012
Questions? 1.800.448.7256

WARNINGS SECTION

Warning: Do not use if tamper - evident seal is broken or missing. Consult a licensed healthcare professional if pregnant, nursing or if symptoms worsen or persist for more than a few days. Keep out of reach of children.

OTC - PREGNANCY OR BREAST FEEDING SECTION

Consult a licensed healthcare professional if pregnant, nursing or if symptoms worsen or persist for more than a few days.

OTC - KEEP OUT OF REACH OF CHILDREN SECTION

Keep out of reach of children